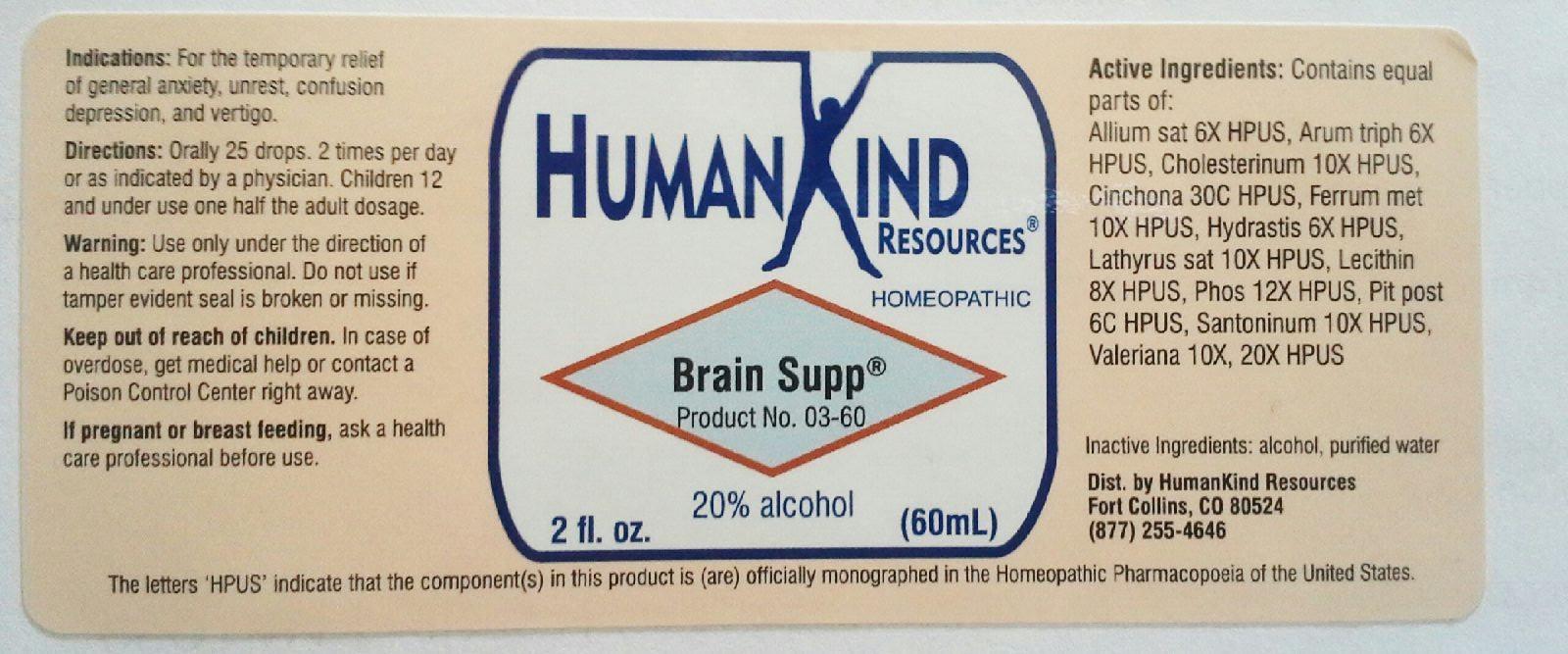 DRUG LABEL: Brain Supp
NDC: 64616-081 | Form: LIQUID
Manufacturer: Vitality Works, Inc.
Category: homeopathic | Type: HUMAN OTC DRUG LABEL
Date: 20251217

ACTIVE INGREDIENTS: GARLIC 6 [hp_X]/1 mL; ARISAEMA TRIPHYLLUM ROOT 6 [hp_X]/1 mL; IRON 10 [hp_X]/1 mL; GOLDENSEAL 6 [hp_X]/1 mL; LATHYRUS SATIVAS SEED 10 [hp_X]/1 mL; EGG PHOSPHOLIPIDS 8 [hp_X]/1 mL; PHOSPHORUS 12 [hp_X]/1 mL; SANTONIN 10 [hp_X]/1 mL; SUS SCROFA PITUITARY GLAND 6 [hp_C]/1 mL; CHOLESTEROL 10 [hp_X]/1 mL; VALERIAN 10 [hp_X]/1 mL; CINCHONA OFFICINALIS BARK 30 [hp_C]/1 mL
INACTIVE INGREDIENTS: ALCOHOL; WATER

Brain Supp

Brain Supp

Allium sat 6X
Arum triph 6X
Cholesterinum 10X
Cinchona 30C
Ferrum met 10X
Hydrastis 6X
Lathyrus sat 10X
Lecithin 8X
Phos 12X
Pit post 6C
Santoninum 10X
Valeriana 20X

Brain Supp

Alcohol, Purified Water

Brain Supp

Use only under the direction of a health care professional. Do not use if tamper evident seal is broken or missing.

Brain Supp

Keep out of reach of children. In case of overdose, get medical help or contact a Poison Control Center right away.

Brain Supp

For the temporary relief of general anxiety, unrest, confusion, depression and vertigo

DOSAGE AND ADMINISTRATION

Orally 25 drops, 2 times per day or as indicated by a physician. Children 12 and under use one half the adult dosage

Brain Supp

Supports brain health.